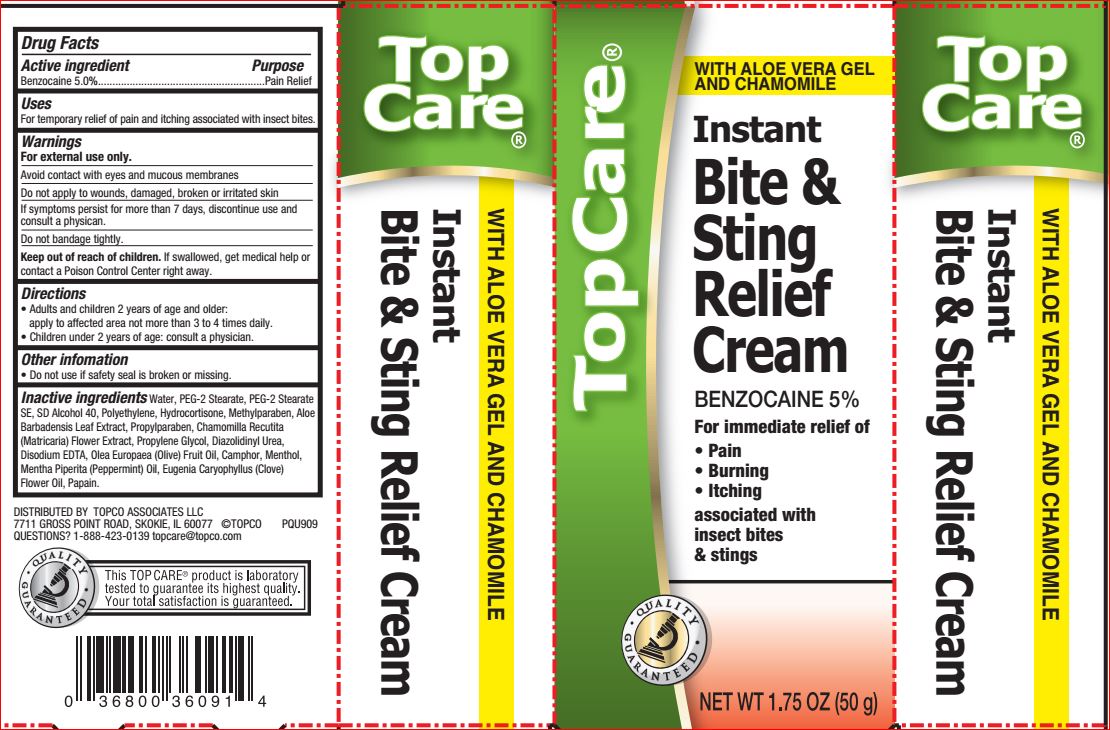 DRUG LABEL: Bite and Sting relief
NDC: 36800-718 | Form: CREAM
Manufacturer: Top care
Category: otc | Type: HUMAN OTC DRUG LABEL
Date: 20180709

ACTIVE INGREDIENTS: Benzocaine 5 g/100 g
INACTIVE INGREDIENTS: Water; PEG-2 Stearate; ALCOHOL; HIGH DENSITY POLYETHYLENE; Hydrocortisone; Methylparaben; ALOE VERA LEAF; Propylparaben; CHAMOMILE; Propylene Glycol; Diazolidinyl Urea; EDETATE DISODIUM; OLIVE OIL; CAMPHOR (SYNTHETIC); Menthol; Peppermint; CLOVE OIL; Papain

Drug Facts

Active ingredients Purpose

Benzocaine 5.00%

Uses

For temporarily relief of pain and itching associated with insect bites

Warning For external use only

When using this product avoid contact with eyes and mucous membranes

Stop use and ask a doctor if condition worsens• symptoms last more than 7 days or clear up and occur again within a few days

Keep out of reach of the children
If product is swallowed, get medical help or contact a Poison Control Center right away
In case of accidental ingestion, seek professional or contact a Poison Control Center immediately.

Direction

Adults and children 2 years of age and older: • apply to the affected area nor mre than 3 to 4 times daily. Children under 2 years of age: consult a doctor

Inactive ingredients

Water
PEG-2 Stearate
PEG-2 Stearate SE
SD Alcohol 40
Polyethylene
Hydrocortisone
Methylparaben
Aloe Barbadensis Leaf Extract
Propylparaben
Chamomilla Recutita (Matricaria) Flower Extract
Propylene Glycol
Diazolidinyl Urea
Disodium EDTA
Olea Europaea (Olive) Fruit Oil
Camphor
Menthol
Mentha Piperita (Peppermint) Oil
Eugenia Caryophyllus (Clove) Flower Oil
Papain